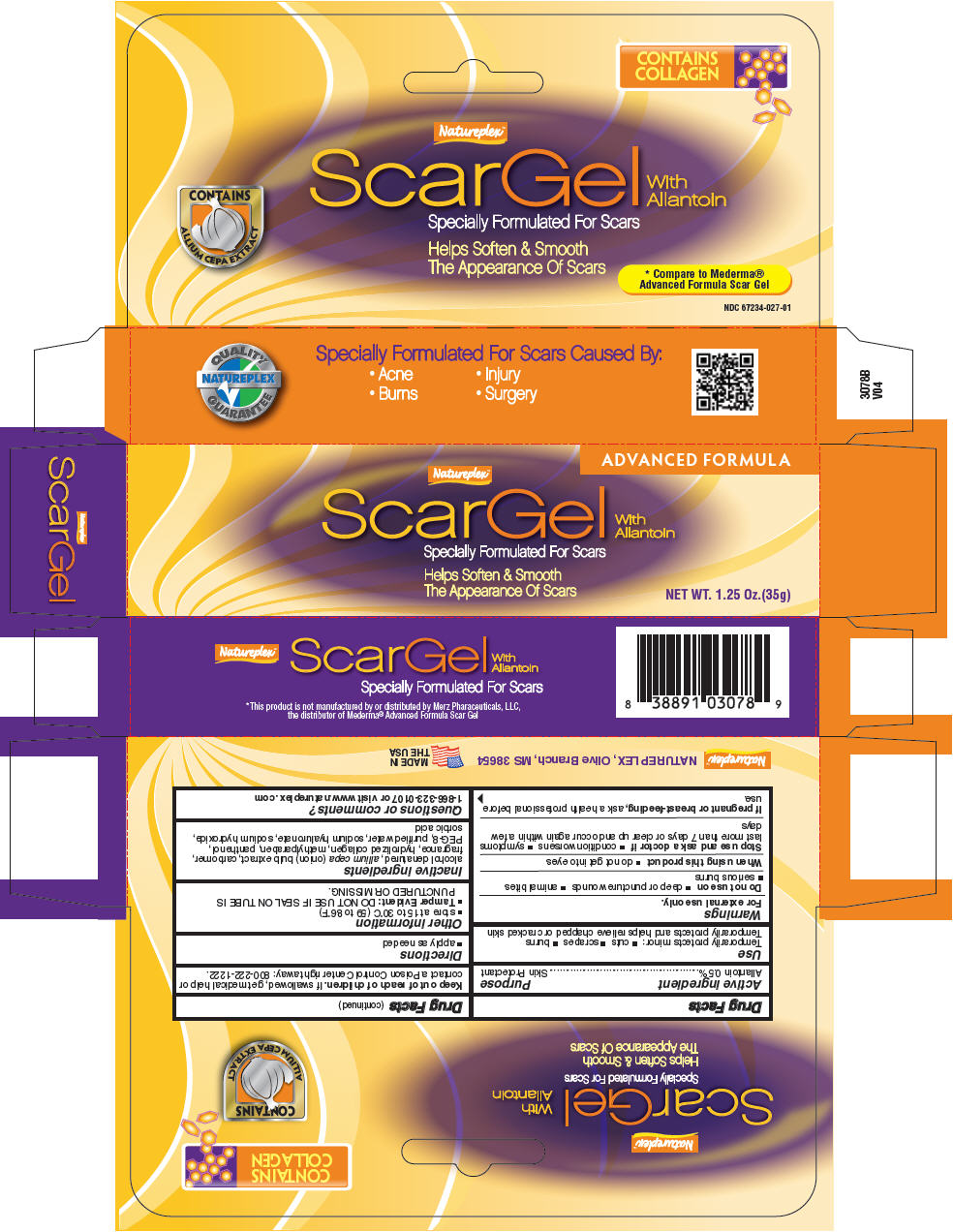 DRUG LABEL: Scar Gel 
NDC: 67234-027 | Form: CREAM
Manufacturer: Natureplex LLC
Category: otc | Type: HUMAN OTC DRUG LABEL
Date: 20241231

ACTIVE INGREDIENTS: ALLANTOIN 0.005 mg/1 g
INACTIVE INGREDIENTS: CARBOMER HOMOPOLYMER TYPE C (ALLYL PENTAERYTHRITOL CROSSLINKED); HUMAN TYPE III COLLAGEN; METHYLPARABEN; ONION; PANTHENOL; POLYETHYLENE GLYCOL 400; WATER; ALCOHOL; HYALURONATE SODIUM; SODIUM HYDROXIDE; SORBIC ACID

Scar Gel
Advanced Formula

Drug Facts

Active ingredient

Allantoin 0.5%

Purpose

Skin Protectant

Use

Temporarily protects minor:

- cuts
- scrapes
- burns

Temporarily protects and helps relieve chapped or cracked skin

Warnings

For external use only.

Do not use on

- deep or puncture wounds
- animal bites
- serious burns

When using this product

- do not get into eyes

Stop use and ask a doctor if

- condition worsens
- symptoms last more than 7 days or clear up and occur again within a few days

PREGNANCY OR BREAST FEEDING

If pregnant or breast-feeding, ask a health professional before use.

Keep out of reach of children. If swallowed, get medical help or contact a Poison Control Center right away: 800-222-1222.

Directions

- apply as needed

Other information

- store at 15 to 30°C (59 to 86°F)
- Tamper Evident: DO NOT USE IF SEAL ON TUBE IS PUNCTURED OR MISSING.

Inactive ingredients

alcohol denatured, allium cepa (onion) bulb extract, carbomer, fragrance, hydrolized collagen, methylparaben, panthenol, PEG-8, purified water, sodium hyaluronate, sodium hydroxide, sorbic acid

Questions or comments?

1-866-323-0107 or visit www.natureplex .com

PRINCIPAL DISPLAY PANEL - 35 g Tube Box

ADVANCED FORMULA

Natureplex™

ScarGel
With
Allantoin
Specially Formulated For Scars

Helps Soften & Smooth
The Appearance Of Scars

NET WT. 1.25 Oz.(35g)